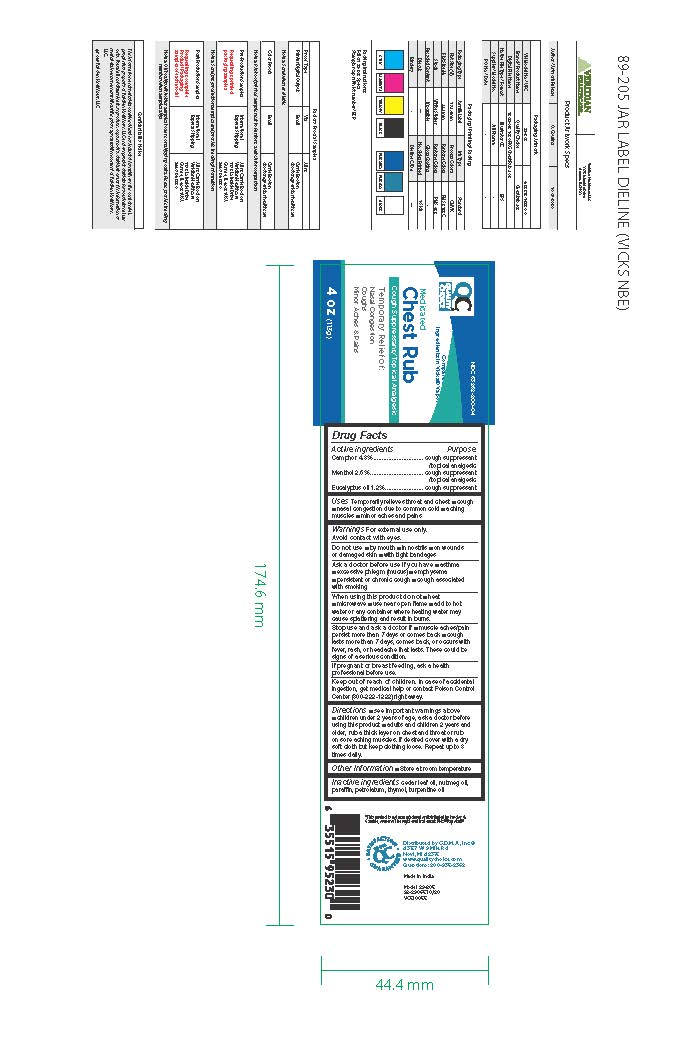 DRUG LABEL: Quality Choice Medicated Chest Rub
NDC: 63868-800 | Form: OINTMENT
Manufacturer: QUALITY CHOICE (Chain Drug Marketing Association)
Category: otc | Type: HUMAN OTC DRUG LABEL
Date: 20251117

ACTIVE INGREDIENTS: EUCALYPTUS OIL 0.012 g/1 g; CAMPHOR (SYNTHETIC) 0.048 g/1 g; MENTHOL 0.026 g/1 g
INACTIVE INGREDIENTS: PETROLATUM; CEDAR LEAF OIL; NUTMEG OIL; THYMOL; TURPENTINE OIL; PARAFFIN

Quality Choice Medicated Chest Rub

Active Ingredients:

Camphor 4.8 %

Menthol 2.6%

Eucalyptus oil 1.2%

PURPOSE

Cough suppressant & topical analgesic,

Cough suppressant

INDICATIONS AND USAGE

- Temporarily relieves throat and chest
- cough
- Nasal congestion due to common cold
- aching muscles
- minor aches and pains

Warnings

For external use only; avoid contact with eyes.

Do not use

- By mouth
- In nostrils
- On wounds or damaged skin
- with tight bandages

Ask A doctor use if you have:

- asthma
- excessive phlegm (mucus)
- emphysema
- Persistent or chronic cough
- cough associated with smoking

When using this product, do not

- heat
- Microware
- Use near open flame
- add to hot water or any container where heating water may cause splattering and result in burns

Stop use and ask a doctor if:

- muscle aches/pain persist more than 7 days or comes back
- cough lasts more than 7 days, comes back or occurs with fever, rash, or headache that lasts. These could be a sign of a serious condition.

If pregnant or breastfeeding

ask a health professional before use

Keep Out Of reach of children

In case of accidental ingestion, get medical help or contact Poison Control Center (800-222-1222) right away.

Directions:

See important warnings above

- children under 2 years of age, ask a doctor before using this product
- Adults and children 2 years and older, rub a thick layer on chest and throat or rub on sore aching muscles. If desired cover with a dry soft cloth but keep clothing loose. Repeat up to 3 times daily.

Other Information

Store at room temperature

Inactive ingredients:

Cedar leaf oil, nutmeg oil, paraffin, petrolatum, thymol, turpentine oil.